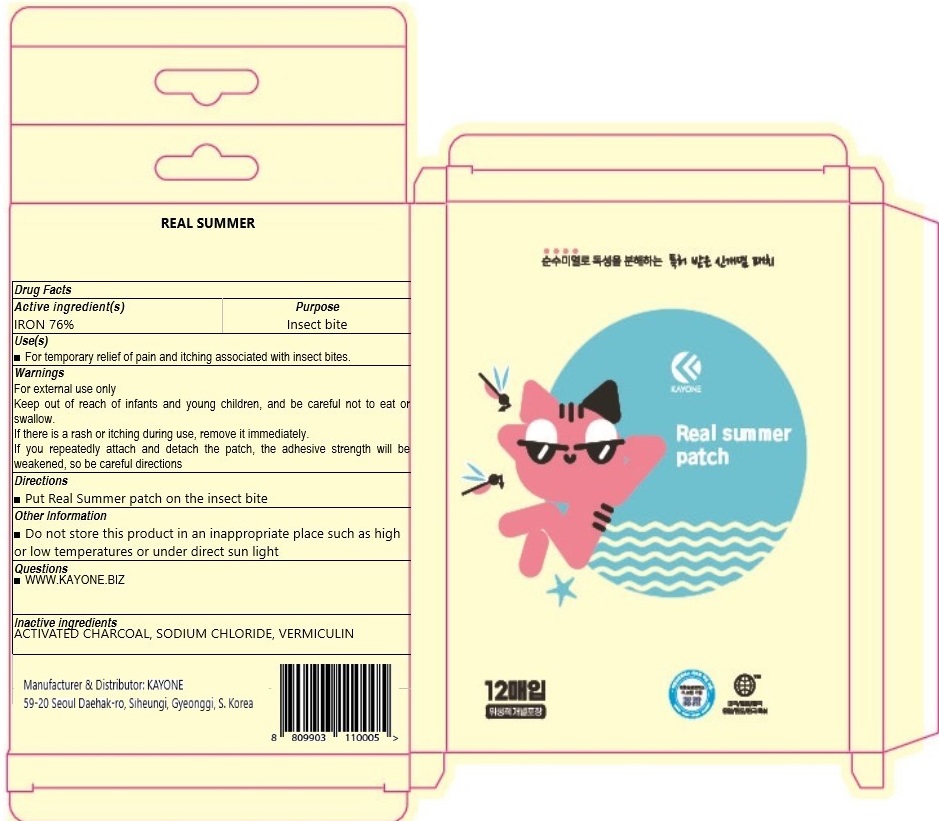 DRUG LABEL: REAL SUMMER
NDC: 69449-1010 | Form: PATCH
Manufacturer: KAYONE
Category: otc | Type: HUMAN OTC DRUG LABEL
Date: 20241209

ACTIVE INGREDIENTS: IRON 0.76 g/1 1
INACTIVE INGREDIENTS: ACTIVATED CHARCOAL; SODIUM CHLORIDE

ACTIVE INGREDIENT

IRON 76%

INACTIVE INGREDIENT

ACTIVATED CHARCOAL, SODIUM CHLORIDE, VERMICULIN

PURPOSE

Insect bite

WARNINGS

For external use only
Keep out of reach of infants and young children, and be careful not to eat or swallow.
If there is a rash or itching during use, remove it immediately.
If you repeatedly attach and detach the patch, the adhesive strength will be weakened, so be careful directions

KEEP OUT OF REACH OF CHILDREN

Keep out of reach of infants and young children, and be careful not to eat or swallow.

Use(s)

■ For temporary relief of pain and itching associated with insect bites.

Directions

■ Put Real Summer patch on the insect bite

Other Information

■ Do not store this product in an inappropriate place such as high or low temperatures or under direct sun light

Questions

■ WWW.KAYONE.BIZ